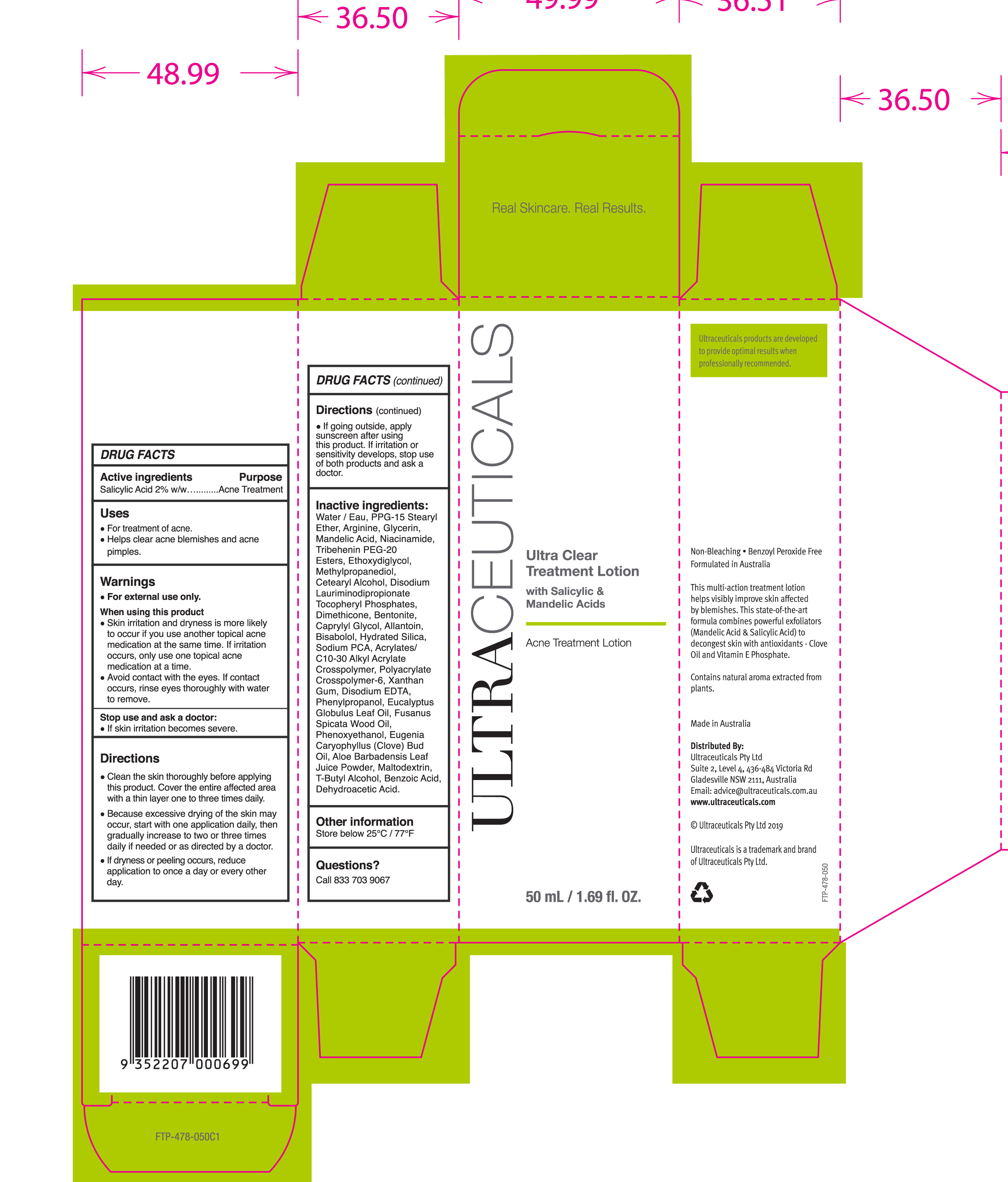 DRUG LABEL: Ultra Clear Treatment
NDC: 73122-126 | Form: LOTION
Manufacturer: Ultraceuticals US LLC
Category: otc | Type: HUMAN OTC DRUG LABEL
Date: 20190926

ACTIVE INGREDIENTS: SALICYLIC ACID 2 g/100 mL
INACTIVE INGREDIENTS: MANDELIC ACID; METHYLPROPANEDIOL; ALLANTOIN; MALTODEXTRIN; CARBOMER INTERPOLYMER TYPE A (ALLYL SUCROSE CROSSLINKED); AMMONIUM ACRYLOYLDIMETHYLTAURATE, DIMETHYLACRYLAMIDE, LAURYL METHACRYLATE AND LAURETH-4 METHACRYLATE COPOLYMER, TRIMETHYLOLPROPANE TRIACRYLATE CROSSLINKED (45000 MPA.S); XANTHAN GUM; PHENYLPROPANOL; EUCALYPTUS OIL; ALOE VERA LEAF; BENZOIC ACID; TERT-BUTYL ALCOHOL; HYDRATED SILICA; SODIUM PYRROLIDONE CARBOXYLATE; EDETATE DISODIUM; CLOVE OIL; SANTALUM SPICATUM OIL; PHENOXYETHANOL; DIETHYLENE GLYCOL MONOETHYL ETHER; CETOSTEARYL ALCOHOL; DISODIUM LAURIMINODIPROPIONATE TOCOPHERYL PHOSPHATES; DIMETHICONE; BENTONITE; CAPRYLYL GLYCOL; LEVOMENOL; WATER; PPG-15 STEARYL ETHER; ARGININE; GLYCERIN; NIACINAMIDE; TRIBEHENIN PEG-20 ESTERS; DEHYDROACETIC ACID

Ultra Clear Treatment Lotion
with salicylic and mandelic acid

Active Ingredients Purpose

Salicylic Acid 2% w/w Acne Treatment

Uses

- For treatment of acne
- Helps clear acne blemishes and acne pimples

KEEP OUT OF REACH OF CHILDREN

Avoid contact with the eyes. If contact occurs, rinse eyes thoroughly with water to remove.

Stop use and ask a doctor:

- If skin irritation becomes severe

Warnings

- For external use only

When using this product

- Skin irritation and dryness is more likely to occur if you use another topical acne medication at the same time. If irritation occurs only use one topical acne medication at a time.

Directions

- Clean the skin thoroughly before applying this product. Cover the entire affected area with a thin layer one to three times daily.
- Because excessive drying of the skin may occur, start with one application daily, then gradually increase to two or three times daily if needed or as directed by a doctor
- If dryness or peeling occurs, reduce application to once a day or every other day.

Inactive ingredients:

Water/Eau, PPG-15 Stearyl Ether, Arginine, Glycerin, Mandelic Acid, Niacinamide, Tribehenin PEG-20 Esters, Ethoxydiglycol, Methylpropanediol, Cetearyl Alcohol, Disodium Laurimodipropionate Tocopheryl Phosphates, Dimethicone, Bentonite, Caprylyl Glycol, Allantoin, Bisabolol, Hydrated Silica, Sodium PCA, Acrylates/C10-30 Alkyl Acrylate Crosspolymer, Polyacrylate Crosspolymer-6 Xanthan Gum, Disodium EDTA, Phenylpropanol, Eucalyptus Globulus Leaf Oil, Fusanus Spicata Wood Oil, Phenoxyethanol, Eugenia Caryophyllus (Clove) Bud Oil, Aloe Barbadensis Leaf Juice Powder, Maltodextrin, T-Butyl Alcohol, Benzoic Acid, Dehydroacetic Acid.

PACKAGE LABEL

Ultraceuticals

Ultra Clear Treatment Lotion

with Salicylic & Mandelic Acid

Acne Treatment Lotion

50mL / 1.69 fl OZ

.